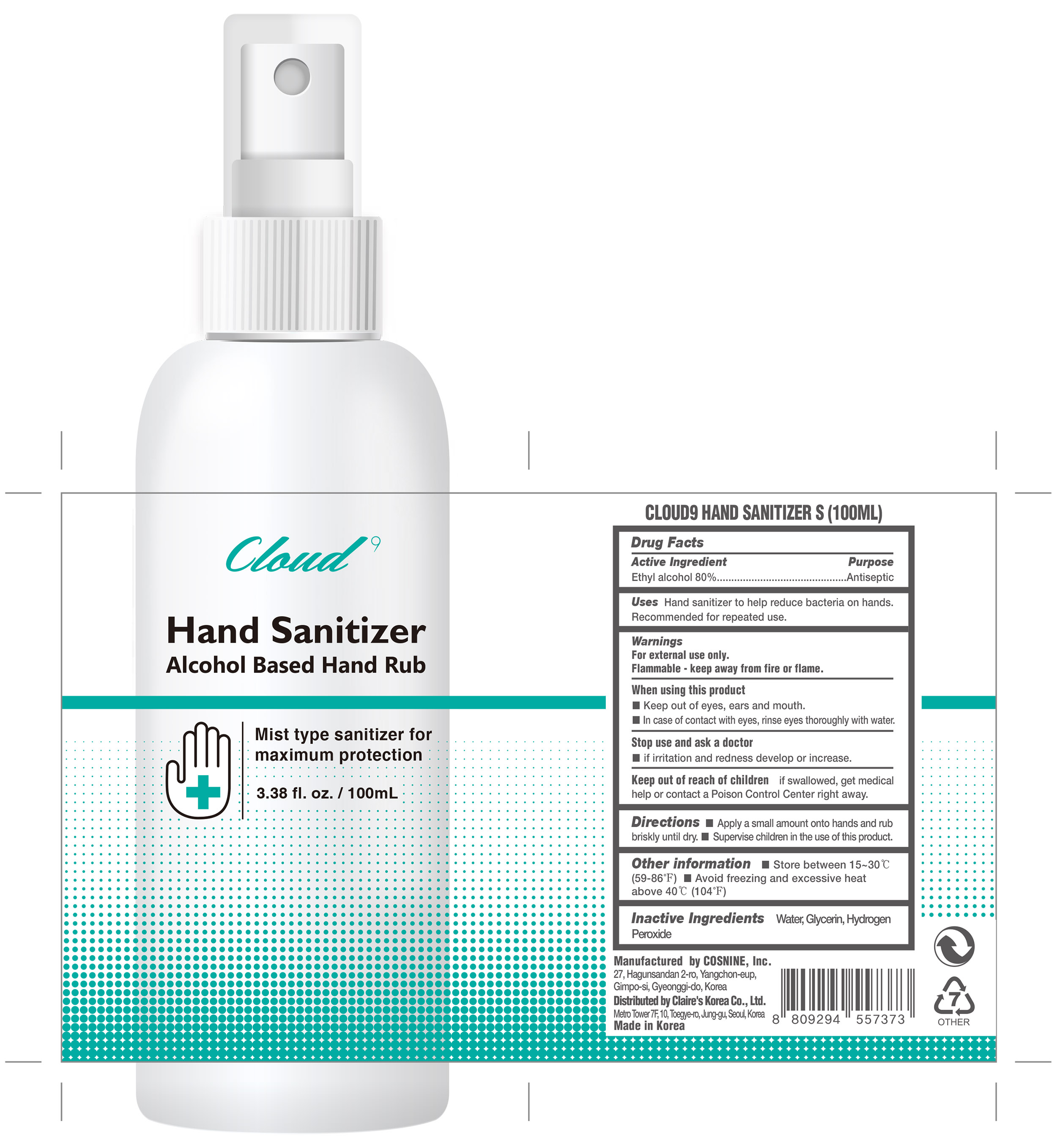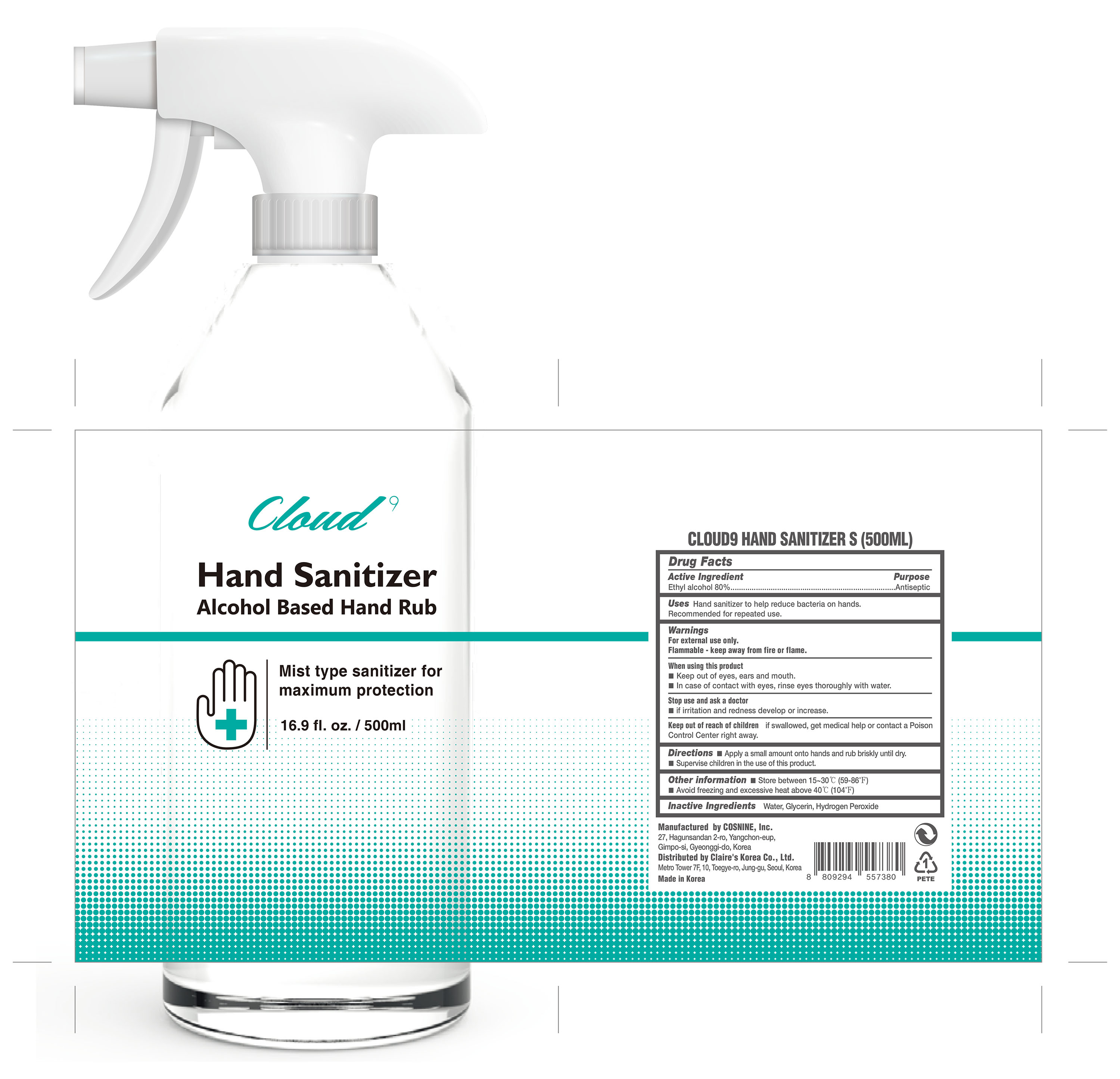 DRUG LABEL: CLOUD9 HAND SANITIZER S
NDC: 73330-0013 | Form: LIQUID
Manufacturer: COSNINE Inc
Category: otc | Type: HUMAN OTC DRUG LABEL
Date: 20200425

ACTIVE INGREDIENTS: ALCOHOL 0.8 mL/1 mL
INACTIVE INGREDIENTS: GLYCERIN; WATER; HYDROGEN PEROXIDE

Active Ingredient(s)

Ethyl alcohol 80%

Purpose

Antiseptic

Uses

Hand sanitizer to help reduce bacteria on hands.
Recommended for repeated use.

Warnings

For external use only.

Flammable - Keep away from fire or flame

When using this product

- Keep out of eyes, ear and mouth.
- In case of contact with eyes, rinse eyes thoroughly with water.

Stop use and ask a doctor

if irritation and redness develop or increase.

Keep out of reach of children

if swallowed, get medical help or contact a Poison Control Center right away.

Directions

- Apply a small amount onto hands and rub briskly until dry.
- Supervise children in the use of this product.

Other information

- Store at 15-30ºC (59-86ºF)
- Avoid freezing and excessive heat above 40ºC (104ºF)

Inactive ingredients

Water, Glycerin, Hydrogen Peroxide

Package Label - Principal Display Panel

500 mL NDC: 73330-0012-1

100 mL NDC: 73330-0012-2